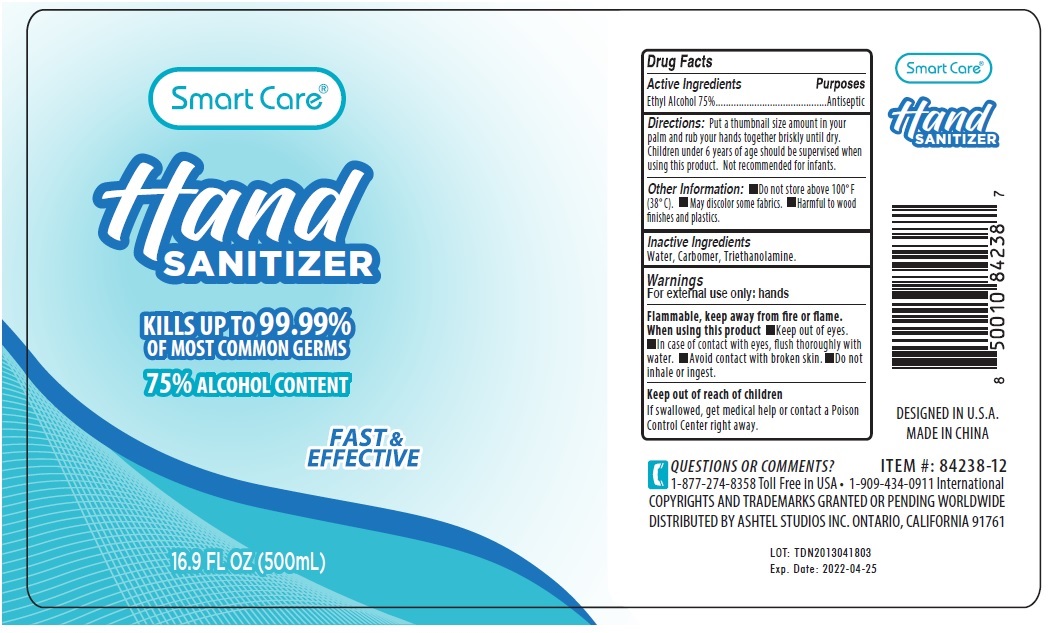 DRUG LABEL: Smart Care Hand Sanitizer 16.9 oz
NDC: 74881-004 | Form: GEL
Manufacturer: Huizhou Baozi Biotechnology Co., Ltd.
Category: otc | Type: HUMAN OTC DRUG LABEL
Date: 20200417

ACTIVE INGREDIENTS: ALCOHOL 75 mL/100 mL
INACTIVE INGREDIENTS: WATER; CARBOMER HOMOPOLYMER, UNSPECIFIED TYPE; TROLAMINE

Smart Care® Hand SANITIZER

Active Ingredients

Ethyl Alcohol 75%

Purposes

Antiseptic

Uses

For external use only: hands

Directions:

Put a thumbnail size amount in your palm and rub your hands together briskly until dry.

Children under 6 years of age should be supervised when using this product.

Not recommended for infants.

Other Information:

• Do not store above 100°F (38°C).

• May discolor some fabrics.

• Harmful to wood finishes and plastics.

Inactive Ingredients

Water, Carbomer, Triethanolamine.

Warnings

For external use only: hands

Flammable, Keep away from fire or flame.

When using this product

• Keep out of eyes.

• In case of contact with eyes, flush thoroughly with water.

• Avoid contact with broken skin.

• Do not inhale or ingest.

Keep out of reach of children

If swallowed, get medical help or contact a Poison Control Center right away.

KILLS UP TO 99.99% OF MOST COMMON GERMS

75% ALCOHOL CONTENT

FAST & EFFECTIVE

QUESTIONS OR COMMENTS?

1-877-274-8358 Toll Free in USA • 1-909-434-0911 International

COPYRIGHTS AND TRADEMARKS GRANTED OR PENDING WORLDWIDE

DISTRIBUTED BY ASHTEL STUDIOS INC. ONTARIO, CALIFORNIA 91761

DESIGNED IN U.S.A

MADE IN CHINA